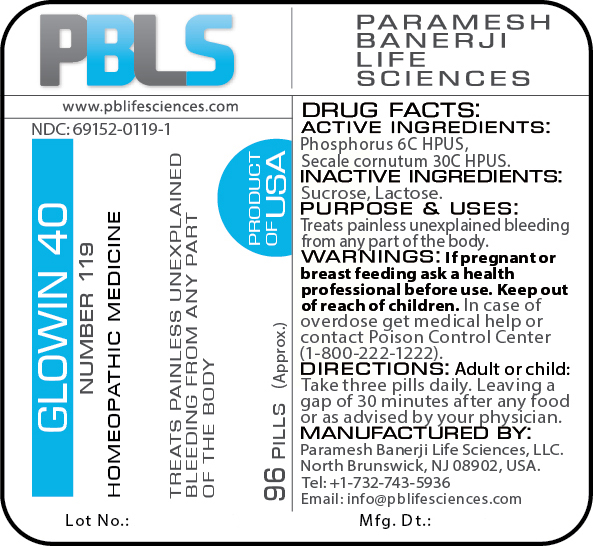 DRUG LABEL: Glowin 40 (Number 119)
NDC: 69152-0119 | Form: PELLET
Manufacturer: Paramesh Banerji Life Sciences LLC
Category: homeopathic | Type: HUMAN OTC DRUG LABEL
Date: 20180613

ACTIVE INGREDIENTS: CLAVICEPS PURPUREA SCLEROTIUM 30 [hp_C]/1 1; PHOSPHORUS 6 [hp_C]/1 1
INACTIVE INGREDIENTS: LACTOSE; SUCROSE

DRUG FACTS: Active Ingredients

Phosphorus 6C HPUS, Secale cornutum 30C HPUS

Inactive Ingredients

Sucrose, Lactose

Purpose

Treats painless unexplained bleeding from any part of the body

Uses

Treats painless unexplained bleeding from any part of the body

Warnings

If pregnant or breast feeding ask a health professional before use.

Keep out of reach of children. In case of overdose, get medical help or contact a Poison Control Center (1-800-222-1222) right away.

Direction

Adult or child: Take three pills daily. Leaving a gap of 30 minutes after any food or as advised by your physician.

Manufactured by

Paramesh Banerji Life Sciences, LLC.

North Brunswick, NJ 08902, USA

Tel: +1-732-743-5936

Email: info@pblifesciences.com

Principal Display Panel

NDC: 69152-0119-1

Glowin 40

Number 119

Homeopathic Medicine

Treats painless unexplained bleeding from any part of the body

96 Pills (Approx.)

Product of USA